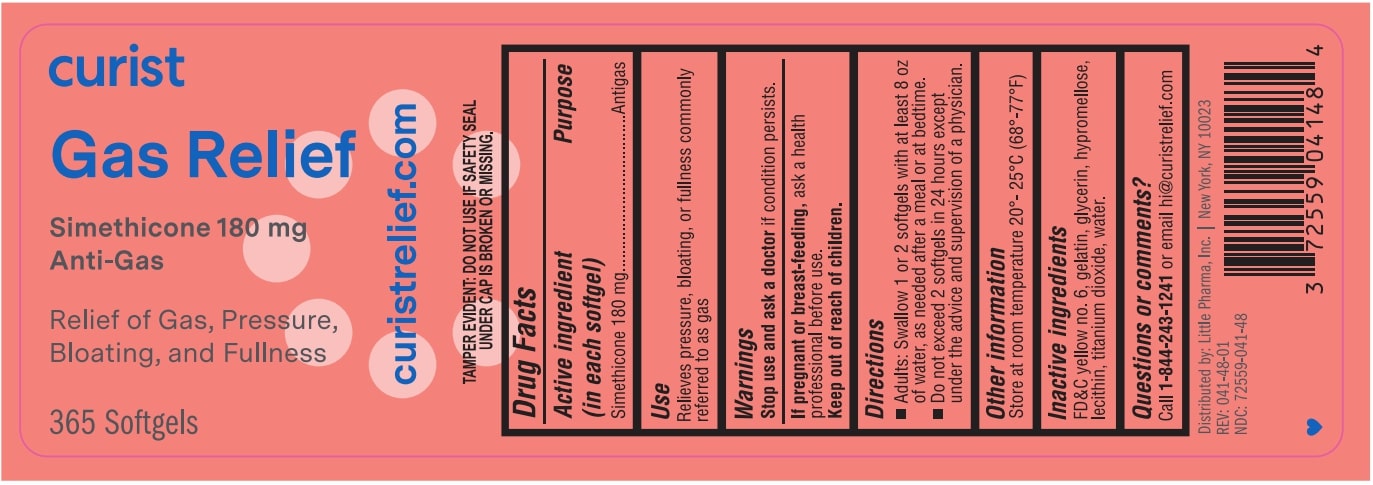 DRUG LABEL: Curist Gas Relief
NDC: 72559-041 | Form: CAPSULE, LIQUID FILLED
Manufacturer: Little Pharma. Inc.
Category: otc | Type: HUMAN OTC DRUG LABEL
Date: 20250706

ACTIVE INGREDIENTS: DIMETHICONE 180 mg/180 mg
INACTIVE INGREDIENTS: FD&C YELLOW NO. 6; GELATIN; WATER; TITANIUM DIOXIDE; HYPROMELLOSES; LECITHIN, SOYBEAN; GLYCERIN

Drug Facts

Active Ingredient (in each softgel)

Simethicone 180 mg

Purpose

Antigas

Warnings

Stop use and ask doctor if condition persists

PREGNANCY OR BREAST FEEDING

If pregant or breast feeding, ask a health profession before use

Keep out of reach of children

Use

Relieves pressure, bloating, or fullness commonly referred to as gas

Directions

- Adults: Swallow 1 or 2 softgels with at least 8 oz of water, as needed after a meal or at bedtime.
- Do not eceed 2 softgels in 24 hours except under the advice and supervision of a physician.

Other information

Store at room temperature 20-25°C (68-77°F)

INACTIVE INGREDIENT

Inactive ingredients FD&C Yellow No. 6, gelatin, glycerin, hypromellose, lecithin, titanium dioxide, water

Questions or Comments?

Call 1-800-243-1241 or email hi@curistrelief.com

Distrbuted by:

Little Pharma, Inc.

New York, NY 10023

PACKAGE LABEL

curist

Gas Relief

Simethicone 180 mg

Anti-Gas

Relief of Gas, Pressure, Bloating, and Fullness

365 Softgels